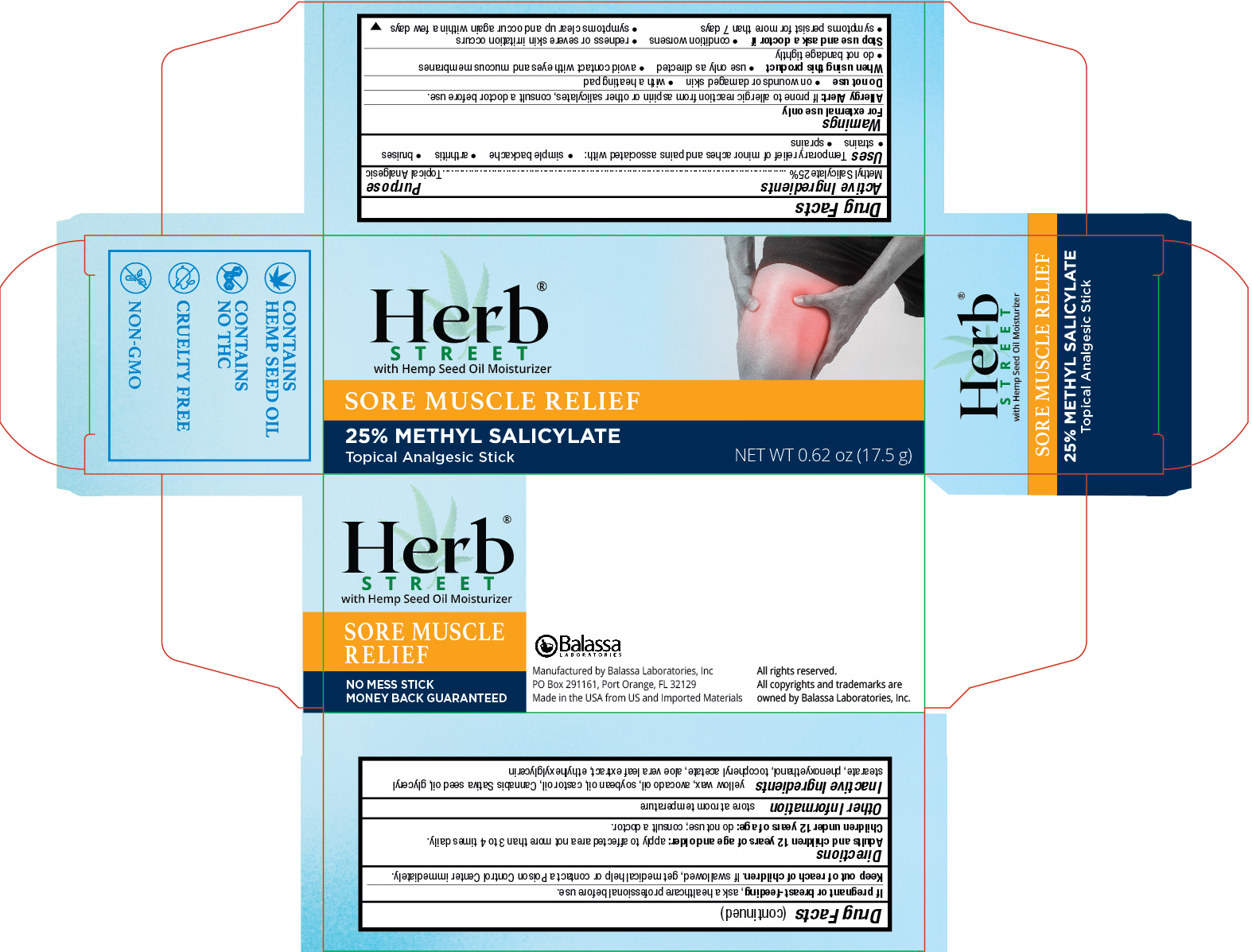 DRUG LABEL: Herb Street Sore Muscle Relief
NDC: 10107-420 | Form: STICK
Manufacturer: Balassa Laboratories Inc.
Category: otc | Type: HUMAN OTC DRUG LABEL
Date: 20241001

ACTIVE INGREDIENTS: METHYL SALICYLATE 0.25 g/1 g
INACTIVE INGREDIENTS: YELLOW WAX; AVOCADO OIL; SOYBEAN OIL; CASTOR OIL; CANNABIS SATIVA SEED OIL; GLYCERYL MONOSTEARATE; PHENOXYETHANOL; .ALPHA.-TOCOPHEROL ACETATE; ALOE VERA LEAF; ETHYLHEXYLGLYCERIN

Herb Street Sore Muscle Relief

Active Ingredient

Methyl Salicylate 25%

Purpose

Topical Analgesic

Uses

Temporary relief of minor aches and pains associated with:

- simple backache
- arthritis
- bruises
- strains
- sprains

Warnings

For external use only

Allergy Alert: If prone to allergic reaction from aspirin or other salicylates, consult a doctor before use.

Do not use

- on wounds or damaged skin
- with a heating pad

When using this product

- use only as directed
- avoid contact with eyes and mucous membranes
- do not bandage tightly

Stop use and ask a doctor if

- condition worsens
- redness or severe skin irritation occurs
- symptoms persist for more than 7 days
- symptoms clear up and occur again within a few days

If pregnant or breast-feeding

ask a healthcare professional before use.

Keep out of reach of children.

If swallowed, get medical help or contact a Poison Control Center right away.

Directions

Adults and children 12 years of age and older:apply to affected area not more than 3 to 4 times daily.
Children under 12 years of age: do not use; consult a doctor.

Other Information

store at room temperature

Inactive Ingredients

yellow wax, avocado oil, soybean oil, castor oil, Cannabis Sativa seed oil, glyceryl stearate, phenoxyethanol, tocopheryl acetate, aloe vera leaf extract, ethylhexylglycerin

PRINCIPAL DISPLAY PANEL - 17.5 g Tube in Carton

Herb Street with Hemp Seed Oil Moisturizer

Sore Muscle Relief

25% Methyl Salicylate

Topical Analgesic Stick

NET WT 0.62 oz (17.5 g)

No Mess Stick

Money Back Guranteed

Manufactured by Balassa Laboratories, Inc.

PO Box 291161, Port Orange, FL 32129

Made in the USA from US and Imported Materials

All rights reserved.

All copyrights and trademarks are owned by Balassa Laboratories, Inc.